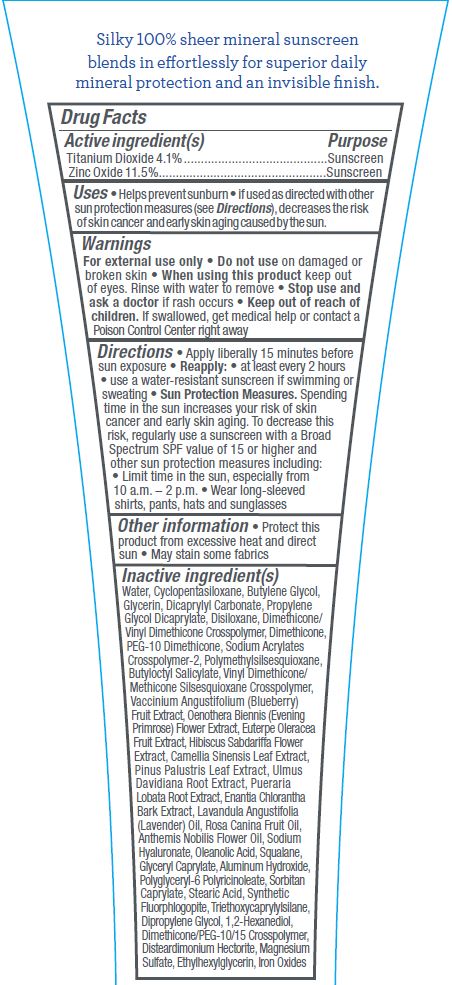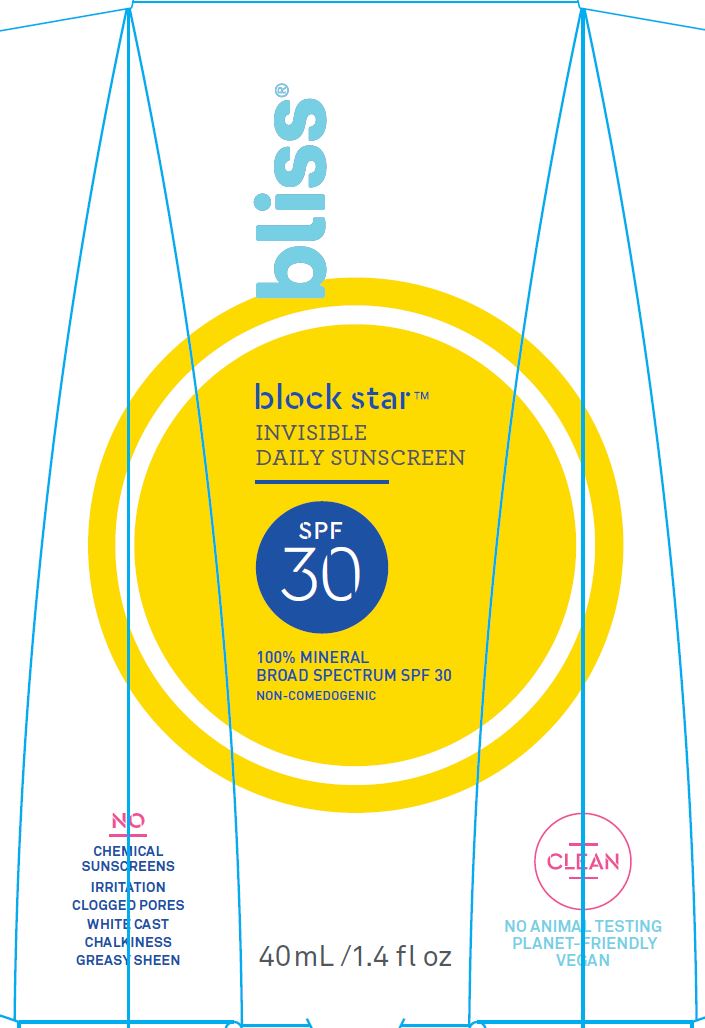 DRUG LABEL: BLISS BLOCK STAR - INVISIBLE DAILY SUNSCREEN
NDC: 67038-200 | Form: LOTION
Manufacturer: Bliss Products Holdings LLC
Category: otc | Type: HUMAN OTC DRUG LABEL
Date: 20211231

ACTIVE INGREDIENTS: TITANIUM DIOXIDE 4.1 g/100 mL; ZINC OXIDE 11.5 g/100 mL
INACTIVE INGREDIENTS: WATER; CYCLOMETHICONE 5; BUTYLENE GLYCOL; GLYCERIN; DICAPRYLYL CARBONATE; PROPYLENE GLYCOL DICAPRYLATE; HEXAMETHYLDISILOXANE; MAGNESIUM SULFATE ANHYDROUS; ETHYLHEXYLGLYCERIN; FERROUS OXIDE; SODIUM POLYACRYLATE (8000 MW); DIMETHICONE/VINYL DIMETHICONE CROSSPOLYMER (SOFT PARTICLE); DIMETHICONE; PEG-10 DIMETHICONE (600 CST); POLYMETHYLSILSESQUIOXANE (11 MICRONS); BUTYLOCTYL SALICYLATE; VINYL DIMETHICONE/METHICONE SILSESQUIOXANE CROSSPOLYMER; BLUEBERRY; OENOTHERA BIENNIS FLOWER; EUTERPE OLERACEA WHOLE; HIBISCUS SABDARIFFA FLOWER; GREEN TEA LEAF; PINUS PALUSTRIS LEAF; ULMUS DAVIDIANA ROOT; PUERARIA MONTANA VAR. LOBATA ROOT; ANNICKIA CHLORANTHA BARK; LAVENDER OIL; ROSA CANINA FRUIT OIL; CHAMAEMELUM NOBILE FLOWER OIL; HYALURONATE SODIUM; OLEANOLIC ACID; SQUALANE; GLYCERYL CAPRYLATE; ALUMINUM HYDROXIDE; POLYGLYCERYL-3 PENTARICINOLEATE; SORBITAN MONOCAPRYLATE; STEARIC ACID; TRIETHOXYCAPRYLYLSILANE; DIPROPYLENE GLYCOL; 1,2-HEXANEDIOL; DIMETHICONE/PEG-10/15 CROSSPOLYMER; DISTEARDIMONIUM HECTORITE

BLISS BLOCK STAR - INVISIBLE DAILY SUNSCREEN SPF-30

ACTIVE INGREDIENTS

Titanium Dioxide 4.1%
Zinc Oxide 11.5%

PURPOSE

Sunscreen

USES

- Helps prevent sunburn
- if used as directed with other sun protection measures (see Directions), decreases the risk of skin cancer and early skin aging caused by the sun.

WARNINGS

- For external use only
- Do not use on damaged or broken skin
- When using this product keep out of eyes. Rinse with water to remove
- Stop use and ask a doctor if rash occurs

Keep out of reach of children. If swallowed, get medical help or contact a Poison Control Center right away

DIRECTIONS

- Apply liberally 15 minutes beforesun exposure
- Reapply:
- at least every 2 hours
- use a water-resistant sunscreen if swimming orsweating

- Sun Protection Measures. Spending time in the sun increases your risk of skin cancer and early skin aging. To decrease this risk, regularly use a sunscreen with a Broad Spectrum SPF value of 15 or higher and other sun protection measures including:
- Limit time in the sun, especially from 10 a.m. – 2 p.m.
- Wear long-sleeved shirts, pants, hats and sunglasses

INACTIVE INGREDIENTS

Water, Cyclopentasiloxane, Butylene Glycol, Glycerin, Dicaprylyl Carbonate, Propylene Glycol Dicaprylate, Disiloxane, Dimethicone/Vinyl Dimethicone Crosspolymer, Dimethicone, PEG-10 Dimethicone, Sodium Acrylates Crosspolymer-2, Polymethylsilsesquioxane, Butyloctyl Salicylate, Vinyl Dimethicone/ Methicone Silsesquioxane Crosspolymer, Vaccinium Angustifolium (Blueberry) Fruit Extract, Oenothera Biennis (Evening
Primrose) Flower Extract, Euterpe Oleracea Fruit Extract, Hibiscus Sabdariffa Flower Extract, Camellia Sinensis Leaf Extract, Pinus Palustris Leaf Extract, Ulmus Davidiana Root Extract, Pueraria Lobata Root Extract, Enantia Chlorantha Bark Extract, Lavandula Angustifolia (Lavender) Oil, Rosa Canina Fruit Oil, Anthemis Nobilis Flower Oil, Sodium Hyaluronate, Oleanolic Acid, Squalane, Glyceryl Caprylate, Aluminum Hydroxide, Polyglyceryl-6 Polyricinoleate, Sorbitan Caprylate, Stearic Acid, Synthetic Fluorphlogopite, Triethoxycaprylylsilane, Dipropylene Glycol, 1,2-Hexanediol, Dimethicone/PEG-10/15 Crosspolymer, Disteardimonium Hectorite, Magnesium Sulfate, Ethylhexylglycerin, Iron Oxides

OTHER INFORMATION

- Protect this product from excessive heat and direct sun
- May stain some fabrics